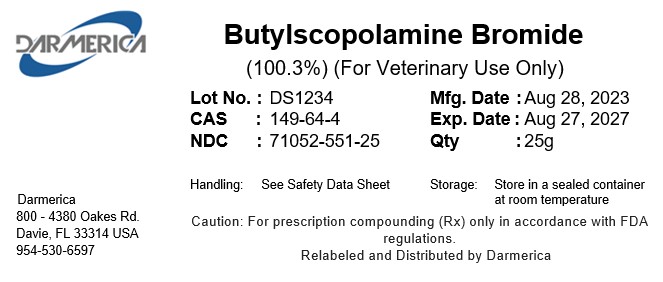 DRUG LABEL: Butylscopolamine Bromide
NDC: 71052-551 | Form: POWDER
Manufacturer: DARMERICA, LLC
Category: other | Type: BULK INGREDIENT - ANIMAL DRUG
Date: 20260105

ACTIVE INGREDIENTS: Butylscopolamine Bromide 1 kg/1 kg

Butylscopolamine Bromide